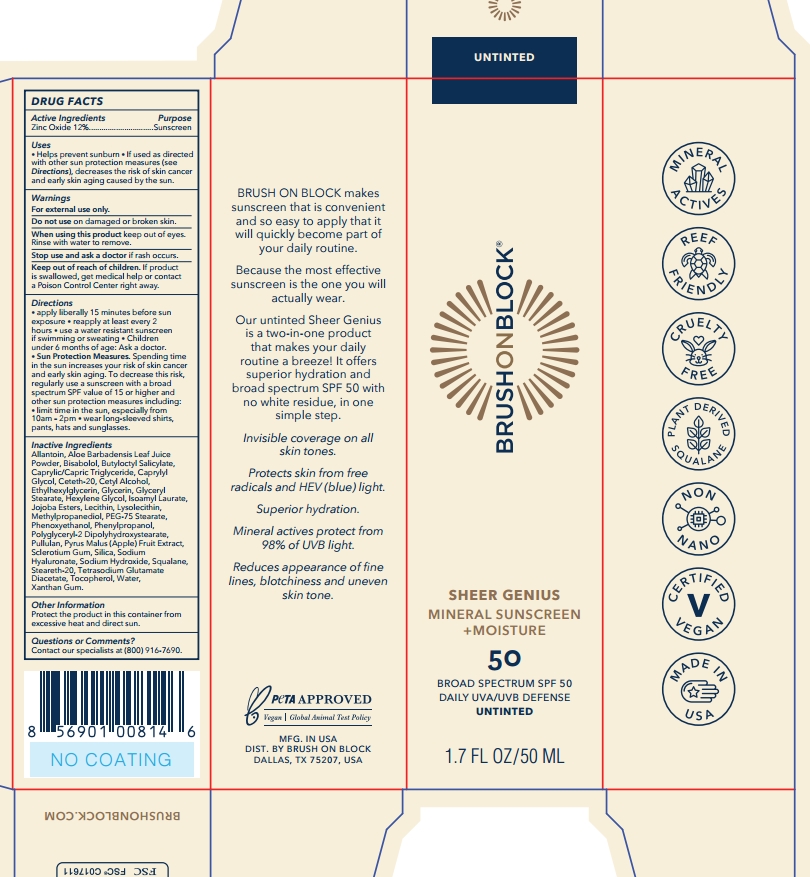 DRUG LABEL: Brush On Block Sheer Genius SPF 50 Mineral Moisture
NDC: 58274-022 | Form: LOTION
Manufacturer: SPF Ventures, LLC
Category: otc | Type: HUMAN OTC DRUG LABEL
Date: 20250204

ACTIVE INGREDIENTS: ZINC OXIDE 12 g/100 mL
INACTIVE INGREDIENTS: SODIUM HYDROXIDE; ALOE BARBADENSIS LEAF JUICE POWDER; CAPRYLIC/CAPRIC TRIGLYCERIDE; CETYL ALCOHOL; HEXYLENE GLYCOL; LYSOPHOSPHATIDYLCHOLINE, SOYBEAN; ETHYLHEXYLGLYCERIN; PHENOXYETHANOL; PHENYLPROPANOL; POLYGLYCERYL-2 DIPOLYHYDROXYSTEARATE; TETRASODIUM GLUTAMATE DIACETATE; TOCOPHEROL; GLYCERIN; GLYCERYL STEARATE; ISOAMYL LAURATE; PEG-75 STEARATE; JOJOBA OIL, RANDOMIZED; SQUALANE; PYRUS MALUS (APPLE) FRUIT; SODIUM HYALURONATE; XANTHAN GUM; METHYLPROPANEDIOL; CAPRYLYL GLYCOL; BISABOLOL; PULLULAN; SCLEROTIUM GUM; SILICA; SODIUM CITRATE; STEARETH-20; WATER; BUTYLOCTYL SALICYLATE; ALLANTOIN; CETETH-20; LECITHIN, SOYBEAN

Brush On Block Sheer Genius SPF 50 Mineral + Moisture

Active Ingredient

Zinc Oxide 12%

Purpose

Sunscreen

Uses

- Helps prevent sunburn
- If used as directed with other sun protection measures (see Directions), decreases the risk of skin cance and early skin aging caused by the sun.

Warnings

For external use only

Do not use on damaged or broken skin.

When using this product keep out of eyes. Rinse with water to remove.

Stop use and ask a doctor if rash occurs.

Keep out of reach of children，If product is swallowed, get medical help or contact a Poison Control Center right away.

Directions

- Apply liberally 15 minutes before sun exposure
- Reapply: After 80 minutes of swimming or sweating; Immediately after towel drying; At least every 2 hours.

Sun Protection Measures. Spending time in the sun increases your risk of skin cance and early skin aging. To decrease this risk, regularly use a sunscreen with a broad spectrum SPF value of 15 or higher and other sun protection measures including:Limit time in the sun especially from 10am-2pm; Wear long-sleeved shirts, pants, hats and subglasses; Children under 6 months: ask a doctor.

Inactive ingredients

Allantoin

Aloe Barbadensis Leaf Juice Powder

Bisabolol

Butyloctyl Salicylate

Caprylic/Capric Triglyceride

Caprylyl Glycol

Ceteth-20

Cetyl Alcohol

Ethylhexylglycerin

Glycerin

Glyceryl Stearate

Hexylene Glycol

Isoamyl Laurate

Jojoba Esters

Lecithin

Lysolecithin

Methylpropanediol

PEG-75 Stearate

Phenoxyethanol

Phenylpropanol

Polyglyceryl-2 Diplolyhydroxystearate

Pullulan

Pyrus Malus (Apple) Fruit Extract

Sclerotium Gum

Silica

Sodium Citrate

Sodium Hyaluronate

Sodium Hydroxide

Squalane

Steareth-20

Tetrasodium Glutamate Diacetate

Tocopherol

Water

Xanthan Gum

Other Information

Protect the product in this container from excessive heat and direct sun.